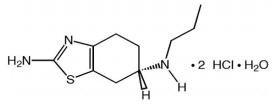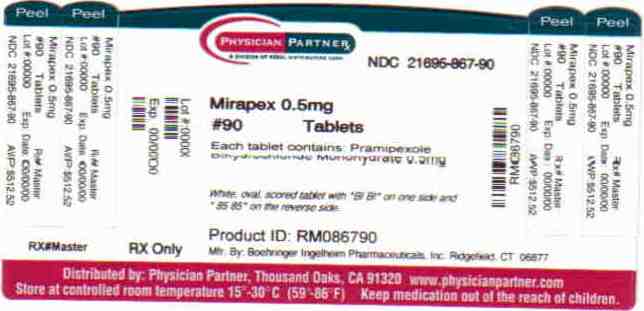 DRUG LABEL: Mirapex
NDC: 21695-867 | Form: TABLET
Manufacturer: Rebel Distributors Corp
Category: prescription | Type: HUMAN PRESCRIPTION DRUG LABEL
Date: 20101229

ACTIVE INGREDIENTS: pramipexole dihydrochloride 0.500 mg/1 1
INACTIVE INGREDIENTS: mannitol; starch, corn; colloidal silicon dioxide; povidone; magnesium stearate

Mirapex® (pramipexole dihydrochloride)
0.125 mg, 0.25 mg, 0.5 mg, 0.75 mg, 1 mg, and 1.5 mg Tablets

Prescribing Information

DESCRIPTION

MIRAPEX tablets contain pramipexole, a nonergot dopamine agonist. The chemical name of pramipexole dihydrochloride is (S)-2-amino-4,5,6,7-tetrahydro-6-(propylamino)benzothiazole dihydrochloride monohydrate. Its empirical formula is C10 H17 N3 S • 2HCl • H2O, and its molecular weight is 302.27.

The structural formula is:

Pramipexole dihydrochloride is a white to off-white powder substance. Melting occurs in the range of 296°C to 301°C, with decomposition. Pramipexole dihydrochloride is more than 20% soluble in water, about 8% in methanol, about 0.5% in ethanol, and practically insoluble in dichloromethane.

MIRAPEX tablets, for oral administration, contain 0.125 mg, 0.25 mg, 0.5 mg, 0.75 mg, 1 mg, or 1.5 mg of pramipexole dihydrochloride monohydrate. Inactive ingredients consist of mannitol, cornstarch, colloidal silicon dioxide, povidone, and magnesium stearate.

CLINICAL PHARMACOLOGY

Mechanism of Action

Pramipexole is a nonergot dopamine agonist with high relative in vitro specificity and full intrinsic activity at the D2 subfamily of dopamine receptors, binding with higher affinity to D3 than to D2 or D4 receptor subtypes.

Parkinson’s Disease: The precise mechanism of action of pramipexole as a treatment for Parkinson's disease is unknown, although it is believed to be related to its ability to stimulate dopamine receptors in the striatum. This conclusion is supported by electrophysiologic studies in animals that have demonstrated that pramipexole influences striatal neuronal firing rates via activation of dopamine receptors in the striatum and the substantia nigra, the site of neurons that send projections to the striatum. The relevance of D3 receptor binding in Parkinson’s disease is unknown.

Restless Legs Syndrome (RLS): The precise mechanism of action of Mirapex® (pramipexole dihydrochloride) tablets as a treatment for Restless Legs Syndrome (RLS) is unknown. Although the pathophysiology of RLS is largely unknown, neuropharmacological evidence suggests primary dopaminergic system involvement. Positron Emission Tomographic (PET) studies suggest that a mild striatal presynaptic dopaminergic dysfunction may be involved in the pathogenesis of RLS.

Pharmacokinetics

Pramipexole displays linear pharmacokinetics over the clinical dosage range. Its terminal half-life is about 8 hours in young healthy volunteers and about 12 hours in elderly volunteers (see CLINICAL PHARMACOLOGY, Pharmacokinetics in Special Populations). Steady-state concentrations are achieved within 2 days of dosing.

Absorption

Pramipexole is rapidly absorbed, reaching peak concentrations in approximately 2 hours. The absolute bioavailability of pramipexole is greater than 90%, indicating that it is well absorbed and undergoes little presystemic metabolism. Food does not affect the extent of pramipexole absorption, although the time of maximum plasma concentration (Tmax) is increased by about 1 hour when the drug is taken with a meal.

Distribution

Pramipexole is extensively distributed, having a volume of distribution of about 500 L (coefficient of variation [CV]=20%). It is about 15% bound to plasma proteins. Pramipexole distributes into red blood cells as indicated by an erythrocyte-to-plasma ratio of approximately 2.

Metabolism and Elimination

The terminal half-life of pramipexole is about 8 hours in healthy volunteers and 12 hours in elderly volunteers.

Urinary excretion is the major route of pramipexole elimination, with 90% of a pramipexole dose recovered in urine, almost all as unchanged drug. Nonrenal routes may contribute to a small extent to pramipexole elimination, although no metabolites have been identified in plasma or urine. The renal clearance of pramipexole is approximately 400 mL/min (CV=25%), approximately three times higher than the glomerular filtration rate. Thus, pramipexole is secreted by the renal tubules, probably by the organic cation transport system.

Pharmacodynamics

In a clinical trial with healthy volunteers, where pramipexole was titrated faster than recommended (every 3 days) up to 4.5 mg per day, an increase in blood pressure and heart rate was observed. Although mean values remained within normal reference ranges throughout the study, supine systolic blood pressure (SBP), diastolic blood pressure (DBP), and pulse rate for subjects treated with pramipexole generally increased during the up-titration phase, up to 10 mmHg, 7 mmHg, and 10 bpm higher than placebo, respectively. Higher SBP, DBP, and pulse rates compared to placebo were maintained until the pramipexole doses were tapered; values on the last day of tapering were generally similar to baseline values. Such effects have not been observed in clinical studies with Parkinson’s disease patients, and are most likely due to the forced up-titration every 3 days.

Pharmacokinetics in Special Populations

Because therapy with MIRAPEX tablets is initiated at a low dose and gradually titrated upward according to clinical tolerability to obtain the optimum therapeutic effect, adjustment of the initial dose based on gender, weight, or age is not necessary. However, renal insufficiency, which can cause a large decrease in the ability to eliminate pramipexole, may necessitate dosage adjustment (see CLINICAL PHARMACOLOGY, Renal Insufficiency).

Gender

Pramipexole clearance is about 30% lower in women than in men, but most of this difference can be accounted for by differences in body weight. There is no difference in half-life between males and females.

Age

Pramipexole clearance decreases with age as the half-life and clearance are about 40% longer and 30% lower, respectively, in elderly (aged 65 years or older) compared with young healthy volunteers (aged less than 40 years). This difference is most likely due to the well-known reduction in renal function with age, since pramipexole clearance is correlated with renal function, as measured by creatinine clearance (see CLINICAL PHARMACOLOGY, Renal Insufficiency).

Parkinson's Disease Patients

A cross-study comparison of data suggests that the clearance of pramipexole may be reduced by about 30% in Parkinson's disease patients compared with healthy elderly volunteers. The reason for this difference appears to be reduced renal function in Parkinson's disease patients, which may be related to their poorer general health. The pharmacokinetics of pramipexole were comparable between early and advanced Parkinson's disease patients.

Restless Legs Syndrome Patients

A cross-study comparison of data suggests that the pharmacokinetic profile of pramipexole administered once daily in RLS patients is similar to the pharmacokinetic profile of pramipexole in healthy volunteers.

Pediatric

The pharmacokinetics of pramipexole in the pediatric population have not been evaluated.

Hepatic Insufficiency

The influence of hepatic insufficiency on pramipexole pharmacokinetics has not been evaluated. Because approximately 90% of the recovered dose is excreted in the urine as unchanged drug, hepatic impairment would not be expected to have a significant effect on pramipexole elimination.

Renal Insufficiency

The clearance of pramipexole was about 75% lower in patients with severe renal impairment (creatinine clearance approximately 20 mL/min) and about 60% lower in patients with moderate impairment (creatinine clearance approximately 40 mL/min) compared with healthy volunteers. Also, it took longer to achieve steady state. A lower starting and/or maintenance dose may be appropriate in these patients (see PRECAUTIONS and DOSAGE AND ADMINISTRATION). In patients with varying degrees of renal impairment, pramipexole clearance correlates well with creatinine clearance. Therefore, creatinine clearance can be used as a predictor of the extent of decrease in pramipexole clearance. Pramipexole clearance is extremely low in dialysis patients, as a negligible amount of pramipexole is removed by dialysis. Caution should be exercised when administering pramipexole to patients with renal disease.

CLINICAL STUDIES

Parkinson's Disease

The effectiveness of Mirapex® (pramipexole dihydrochloride) tablets in the treatment of Parkinson's disease was evaluated in a multinational drug development program consisting of seven randomized, controlled trials. Three were conducted in patients with early Parkinson's disease who were not receiving concomitant levodopa, and four were conducted in patients with advanced Parkinson's disease who were receiving concomitant levodopa. Among these seven studies, three studies provide the most persuasive evidence of pramipexole's effectiveness in the management of patients with Parkinson's disease who were and were not receiving concomitant levodopa. Two of these three trials enrolled patients with early Parkinson's disease (not receiving levodopa), and one enrolled patients with advanced Parkinson's disease who were receiving maximally tolerated doses of levodopa.

In all studies, the Unified Parkinson's Disease Rating Scale (UPDRS), or one or more of its subparts, served as the primary outcome assessment measure. The UPDRS is a four-part multi-item rating scale intended to evaluate mentation (part I), Activities of Daily Living (ADL) (part II), motor performance (part III), and complications of therapy (part IV).

Part II of the UPDRS contains 13 questions relating to ADL, which are scored from 0 (normal) to 4 (maximal severity) for a maximum (worst) score of 52. Part III of the UPDRS contains 27 questions (for 14 items) and is scored as described for part II. It is designed to assess the severity of the cardinal motor findings in patients with Parkinson's disease (e.g., tremor, rigidity, bradykinesia, postural instability, etc.), scored for different body regions, and has a maximum (worst) score of 108.

Studies in Patients with Early Parkinson's Disease

Patients (N=599) in the two studies of early Parkinson's disease had a mean disease duration of 2 years, limited or no prior exposure to levodopa (generally none in the preceding 6 months), and were not experiencing the "on-off" phenomenon and dyskinesia characteristic of later stages of the disease.

One of the two early Parkinson's disease studies (N=335) was a double-blind, placebo-controlled, parallel trial consisting of a 7-week dose-escalation period and a 6-month maintenance period. Patients could be on selegiline, anticholinergics, or both, but could not be on levodopa products or amantadine. Patients were randomized to Mirapex® (pramipexole dihydrochloride) tablets or placebo. Patients treated with MIRAPEX tablets had a starting daily dose of 0.375 mg and were titrated to a maximally tolerated dose, but no higher than 4.5 mg/day in three divided doses. At the end of the 6-month maintenance period, the mean improvement from baseline on the UPDRS part II (ADL) total score was 1.9 in the group receiving MIRAPEX tablets and -0.4 in the placebo group, a difference that was statistically significant. The mean improvement from baseline on the UPDRS part III total score was 5.0 in the group receiving MIRAPEX tablets and -0.8 in the placebo group, a difference that was also statistically significant. A statistically significant difference between groups in favor of MIRAPEX tablets was seen beginning at week 2 of the UPDRS part II (maximum dose 0.75 mg/day) and at week 3 of the UPDRS part III (maximum dose 1.5 mg/day).

The second early Parkinson's disease study (N=264) was a double-blind, placebo-controlled, parallel trial consisting of a 6-week dose-escalation period and a 4-week maintenance period. Patients could be on selegiline, anticholinergics, amantadine, or any combination of these, but could not be on levodopa products. Patients were randomized to 1 of 4 fixed doses of MIRAPEX tablets (1.5 mg, 3.0 mg, 4.5 mg, or 6.0 mg per day) or placebo. At the end of the 4-week maintenance period, the mean improvement from baseline on the UPDRS part II total score was 1.8 in the patients treated with MIRAPEX tablets, regardless of assigned dose group, and 0.3 in placebo-treated patients. The mean improvement from baseline on the UPDRS part III total score was 4.2 in patients treated with MIRAPEX tablets and 0.6 in placebo-treated patients. No dose-response relationship was demonstrated. The between-treatment differences on both parts of the UPDRS were statistically significant in favor of MIRAPEX tablets for all doses.

No differences in effectiveness based on age or gender were detected. There were too few non-Caucasian patients to evaluate the effect of race. Patients receiving selegiline or anticholinergics had responses similar to patients not receiving these drugs.

Studies in Patients with Advanced Parkinson's Disease

In the advanced Parkinson's disease study, the primary assessments were the UPDRS and daily diaries that quantified amounts of "on" and "off" time.

Patients in the advanced Parkinson's disease study (N=360) had a mean disease duration of 9 years, had been exposed to levodopa for long periods of time (mean 8 years), used concomitant levodopa during the trial, and had "on-off" periods.

The advanced Parkinson's disease study was a double-blind, placebo-controlled, parallel trial consisting of a 7-week dose-escalation period and a 6-month maintenance period. Patients were all treated with concomitant levodopa products and could additionally be on concomitant selegiline, anticholinergics, amantadine, or any combination. Patients treated with MIRAPEX tablets had a starting dose of 0.375 mg/day and were titrated to a maximally tolerated dose, but no higher than 4.5 mg/day in three divided doses. At selected times during the 6-month maintenance period, patients were asked to record the amount of "off," "on," or "on with dyskinesia" time per day for several sequential days. At the end of the 6-month maintenance period, the mean improvement from baseline on the UPDRS part II total score was 2.7 in the group treated with Mirapex® (pramipexole dihydrochloride) tablets and 0.5 in the placebo group, a difference that was statistically significant. The mean improvement from baseline on the UPDRS part III total score was 5.6 in the group treated with MIRAPEX tablets and 2.8 in the placebo group, a difference that was statistically significant. A statistically significant difference between groups in favor of MIRAPEX tablets was seen at week 3 of the UPDRS part II (maximum dose 1.5 mg/day) and at week 2 of the UPDRS part III (maximum dose 0.75 mg/day). Dosage reduction of levodopa was allowed during this study if dyskinesia (or hallucinations) developed; levodopa dosage reduction occurred in 76% of patients treated with MIRAPEX tablets versus 54% of placebo patients. On average, the levodopa dose was reduced 27%.

The mean number of "off" hours per day during baseline was 6 hours for both treatment groups. Throughout the trial, patients treated with MIRAPEX tablets had a mean of 4 "off" hours per day, while placebo-treated patients continued to experience 6 "off" hours per day.

No differences in effectiveness based on age or gender were detected. There were too few non-Caucasian patients to evaluate the effect of race.

Restless Legs Syndrome

The efficacy of MIRAPEX tablets in the treatment of Restless Legs Syndrome (RLS) was evaluated in a multinational drug development program consisting of 4 randomized, double-blind, placebo-controlled trials. This program included approximately 1000 patients with moderate to severe RLS; patients with RLS secondary to other conditions (e.g., pregnancy, renal failure, and anemia) were excluded. All patients were administered MIRAPEX tablets (0.125 mg, 0.25 mg, 0.5 mg, or 0.75 mg) or placebo once daily 2-3 hours before going to bed. Across the 4 studies, the mean duration of RLS was 4.6 years (range of 0 to 56 years), mean age was approximately 55 years (range of 18 to 81 years), and approximately 66.6% were women.

The two outcome measures used to assess the effect of treatment were the International RLS Rating Scale (IRLS Scale) and a Clinical Global Impression - Improvement (CGI-I) assessment. The IRLS Scale contains 10 items designed to assess the severity of sensory and motor symptoms, sleep disturbance, daytime somnolence, and impact on activities of daily living and mood associated with RLS. The range of scores is 0 to 40, with 0 being absence of RLS symptoms and 40 the most severe symptoms. The CGI-I is designed to assess clinical progress (global improvement) on a 7-point scale.

In Study 1, fixed doses of MIRAPEX tablets were compared to placebo in a study of 12 weeks duration. A total of 344 patients were randomized equally to the 4 treatment groups. Patients treated with MIRAPEX tablets (n=254) had a starting dose of 0.125 mg/day and were titrated to one of the three randomized doses (0.25, 0.5, 0.75 mg/day) in the first three weeks of the study. The mean improvement from baseline on the IRLS Scale total score and the percentage of CGI-I responders for each of the MIRAPEX tablets treatment groups compared to placebo are summarized in Table 1. All treatment groups reached statistically significant superiority compared to placebo for both endpoints. There was no clear evidence of a dose-response across the 3 randomized dose groups.

Table 1 Mean Changes from Baseline to Week 12 in IRLS Score and CGI-I (Study 1)
 | MIRAPEX 0.25 mg | MIRAPEX 0.5 mg | MIRAPEX 0.75 mg | MIRAPEX Total | Placebo
No. Patients | 88 | 79 | 87 | 254 | 85
IRLS score | -13.1 | -13.4 | -14.4 | -13.6 | -9.4
CGI-I responders* | 74.7% | 67.9% | 72.9% | 72.0% | 51.2%
*CGI-I responders = “much improved” and “very much improved”

Study 2 was a randomized-withdrawal study, designed to demonstrate the sustained efficacy of pramipexole for treatment of RLS after a period of six months. RLS patients who responded to Mirapex® (pramipexole dihydrochloride) tablets treatment in a preceding 6-month open label treatment phase (defined as having a CGI-I rating of “very much improved” or “much improved” compared to baseline and an IRLS score of 15 or below) were randomized to receive either continued active treatment (n=78) or placebo (n=69) for 12 weeks. The primary endpoint of this study was time to treatment failure, defined as any worsening on the CGI-I score along with an IRLS Scale total score above 15.

In patients who had responded to 6-month open label treatment with MIRAPEX tablets, the administration of placebo led to a rapid decline in their overall conditions and return of their RLS symptoms. At the end of the 12-week observation period, 85% of patients treated with placebo had failed treatment, compared to 21% treated with blinded pramipexole, a difference that was highly statistically significant. The majority of treatment failures occurred within 10 days of randomization. For the patients randomized, the distribution of doses was: 7 on 0.125 mg, 44 on 0.25 mg, 47 on 0.5 mg, and 49 on 0.75 mg.

Study 3 was a 6-week study, comparing a flexible dose of MIRAPEX tablets to placebo. In this study, 345 patients were randomized in a 2:1 ratio to MIRAPEX tablets or placebo. The mean improvement from baseline on the IRLS Scale total score was -12 for Mirapex-treated patients and -6 for placebo-treated patients. The percentage of CGI-I responders was 63% for Mirapex-treated patients and 32% for placebo-treated patients. The between-group differences were statistically significant for both outcome measures. For the patients randomized to MIRAPEX tablets, the distribution of achieved doses was: 35 on 0.125 mg, 51 on 0.25 mg, 65 on 0.5 mg, and 69 on 0.75 mg.

Study 4 was a 3-week study, comparing 4 fixed doses of MIRAPEX tablets, 0.125 mg, 0.25 mg, 0.5 mg, and 0.75 mg, to placebo. Approximately 20 patients were randomized to each of the 5 dose groups. The mean improvement from baseline on the IRLS Scale total score and the percentage of CGI-I responders for each of the MIRAPEX tablets treatment groups compared to placebo are summarized in Table 2. In this study, the 0.125 mg dose group was not significantly different from placebo. On average, the 0.5 mg dose group performed better than the 0.25 mg dose group, but there was no difference between the 0.5 mg and 0.75 mg dose groups.

Table 2 Mean Changes from Baseline to Week 3 in IRLS Score and CGI-I (Study 4)
 | MIRAPEX 0.125 mg | MIRAPEX 0.25 mg | MIRAPEX 0.5 mg | MIRAPEX 0.75 mg | MIRAPEX Total | Placebo
No. Patients | 21 | 22 | 22 | 21 | 86 | 21
IRLS score | -11.7 | -15.3 | -17.6 | -15.2 | -15.0 | -6.2
CGI-I responders* | 61.9% | 68.2% | 86.4% | 85.7% | 75.6% | 42.9%
*CGI-I responders = “much improved” and “very much improved”

No differences in effectiveness based on age or gender were detected. There were too few non-Caucasian patients to evaluate the effect of race.

INDICATIONS AND USAGE

Parkinson's Disease

Mirapex® (pramipexole dihydrochloride) tablets are indicated for the treatment of the signs and symptoms of idiopathic Parkinson's disease.

The effectiveness of MIRAPEX tablets was demonstrated in randomized, controlled trials in patients with early Parkinson's disease who were not receiving concomitant levodopa therapy as well as in patients with advanced disease on concomitant levodopa (see CLINICAL STUDIES).

Restless Legs Syndrome

MIRAPEX tablets are indicated for the treatment of moderate-to-severe primary Restless Legs Syndrome (RLS).

Key diagnostic criteria for RLS are: an urge to move the legs usually accompanied or caused by uncomfortable and unpleasant leg sensations; symptoms begin or worsen during periods of rest or inactivity such as lying or sitting; symptoms are partially or totally relieved by movement such as walking or stretching at least as long as the activity continues; and symptoms are worse or occur only in the evening or night. Difficulty falling asleep may frequently be associated with symptoms of RLS.

CONTRAINDICATIONS

MIRAPEX tablets are contraindicated in patients who have demonstrated hypersensitivity to the drug or its ingredients.

WARNINGS

Falling Asleep During Activities of Daily Living

Patients treated with Mirapex® (pramipexole dihydrochloride) tablets have reported falling asleep while engaged in activities of daily living, including the operation of motor vehicles which sometimes resulted in accidents. Although many of these patients reported somnolence while on MIRAPEX tablets, some perceived that they had no warning signs such as excessive drowsiness, and believed that they were alert immediately prior to the event. Some of these events had been reported as late as one year after the initiation of treatment.

Somnolence is a common occurrence in patients receiving MIRAPEX tablets at doses above 1.5 mg/day (0.5 mg TID) for Parkinson’s disease. In controlled clinical trials in RLS, patients treated with MIRAPEX tablets at doses of 0.25-0.75 mg once a day, the incidence of somnolence was 6% compared to an incidence of 3% for placebo-treated patients (see ADVERSE EVENTS, Table 5). Many clinical experts believe that falling asleep while engaged in activities of daily living always occurs in a setting of pre-existing somnolence, although patients may not give such a history. For this reason, prescribers should continually reassess patients for drowsiness or sleepiness, especially since some of the events occur well after the start of treatment. Prescribers should also be aware that patients may not acknowledge drowsiness or sleepiness until directly questioned about drowsiness or sleepiness during specific activities.

Before initiating treatment with MIRAPEX tablets, patients should be advised of the potential to develop drowsiness and specifically asked about factors that may increase the risk with MIRAPEX tablets such as concomitant sedating medications, the presence of sleep disorders, and concomitant medications that increase pramipexole plasma levels (e.g., cimetidine - see PRECAUTIONS, Drug Interactions). If a patient develops significant daytime sleepiness or episodes of falling asleep during activities that require active participation (e.g., conversations, eating, etc.), MIRAPEX tablets should ordinarily be discontinued. If a decision is made to continue MIRAPEX tablets, patients should be advised to not drive and to avoid other potentially dangerous activities. While dose reduction clearly reduces the degree of somnolence, there is insufficient information to establish that dose reduction will eliminate episodes of falling asleep while engaged in activities of daily living.

Symptomatic Hypotension

Dopamine agonists, in clinical studies and clinical experience, appear to impair the systemic regulation of blood pressure, with resulting orthostatic hypotension, especially during dose escalation. Parkinson's disease patients, in addition, appear to have an impaired capacity to respond to an orthostatic challenge. For these reasons, both Parkinson's disease patients and RLS patients being treated with dopaminergic agonists ordinarily require careful monitoring for signs and symptoms of orthostatic hypotension, especially during dose escalation, and should be informed of this risk (see PRECAUTIONS, Information for Patients).

In clinical trials of pramipexole, however, and despite clear orthostatic effects in normal volunteers, the reported incidence of clinically significant orthostatic hypotension was not greater among those assigned to Mirapex® (pramipexole dihydrochloride) tablets than among those assigned to placebo. This result, especially with the higher doses used in Parkinson’s disease, is clearly unexpected in light of the previous experience with the risks of dopamine agonist therapy.

While this finding could reflect a unique property of pramipexole, it might also be explained by the conditions of the study and the nature of the population enrolled in the clinical trials. Patients were very carefully titrated, and patients with active cardiovascular disease or significant orthostatic hypotension at baseline were excluded. Also, clinical trials in patients with RLS did not incorporate orthostatic challenges with intensive blood pressure monitoring done in close temporal proximity to dosing.

Hallucinations

In the three double-blind, placebo-controlled trials in early Parkinson's disease, hallucinations were observed in 9% (35 of 388) of patients receiving MIRAPEX tablets, compared with 2.6% (6 of 235) of patients receiving placebo. In the four double-blind, placebo-controlled trials in advanced Parkinson's disease, where patients received MIRAPEX tablets and concomitant levodopa, hallucinations were observed in 16.5% (43 of 260) of patients receiving MIRAPEX tablets compared with 3.8% (10 of 264) of patients receiving placebo. Hallucinations were of sufficient severity to cause discontinuation of treatment in 3.1% of the early Parkinson's disease patients and 2.7% of the advanced Parkinson's disease patients compared with about 0.4% of placebo patients in both populations.

Age appears to increase the risk of hallucinations attributable to pramipexole. In the early Parkinson's disease patients, the risk of hallucinations was 1.9 times greater than placebo in patients younger than 65 years and 6.8 times greater than placebo in patients older than 65 years. In the advanced Parkinson's disease patients, the risk of hallucinations was 3.5 times greater than placebo in patients younger than 65 years and 5.2 times greater than placebo in patients older than 65 years.

In the RLS clinical program, one pramipexole-treated patient (of 889) reported hallucinations; this patient discontinued treatment and the symptoms resolved.

PRECAUTIONS

Rhabdomyolysis

A single case of rhabdomyolysis occurred in a 49-year-old male with advanced Parkinson's disease treated with MIRAPEX tablets. The patient was hospitalized with an elevated CPK (10,631 IU/L). The symptoms resolved with discontinuation of the medication.

Renal

Since pramipexole is eliminated through the kidneys, caution should be exercised when prescribing Mirapex® (pramipexole dihydrochloride) tablets to patients with renal insufficiency (see DOSAGE AND ADMINISTRATION).

Dyskinesia

MIRAPEX tablets may potentiate the dopaminergic side effects of levodopa and may cause or exacerbate preexisting dyskinesia. Decreasing the dose of levodopa may ameliorate this side effect.

Retinal Pathology in Albino Rats

Pathologic changes (degeneration and loss of photoreceptor cells) were observed in the retina of albino rats in the 2-year carcinogenicity study. While retinal degeneration was not diagnosed in pigmented rats treated for 2 years, a thinning in the outer nuclear layer of the retina was slightly greater in rats given drug compared with controls. Evaluation of the retinas of albino mice, monkeys, and minipigs did not reveal similar changes. The potential significance of this effect in humans has not been established, but cannot be disregarded because disruption of a mechanism that is universally present in vertebrates (i.e., disk shedding) may be involved (see ANIMAL TOXICOLOGY).

Events Reported with Dopaminergic Therapy

Although the events enumerated below may not have been reported in association with the use of pramipexole in its development program, they are associated with the use of other dopaminergic drugs. The expected incidence of these events, however, is so low that even if pramipexole caused these events at rates similar to those attributable to other dopaminergic therapies, it would be unlikely that even a single case would have occurred in a cohort of the size exposed to pramipexole in studies to date.

Withdrawal-Emergent Hyperpyrexia and Confusion

Although not reported with pramipexole in the clinical development program, a symptom complex resembling the neuroleptic malignant syndrome (characterized by elevated temperature, muscular rigidity, altered consciousness, and autonomic instability), with no other obvious etiology, has been reported in association with rapid dose reduction, withdrawal of, or changes in antiparkinsonian therapy.

Fibrotic Complications

Although not reported with pramipexole in the clinical development program, cases of retroperitoneal fibrosis, pulmonary infiltrates, pleural effusion, and pleural thickening, pericarditis, and cardiac valvulopathy have been reported in some patients treated with ergot-derived dopaminergic agents. While these complications may resolve when the drug is discontinued, complete resolution does not always occur.

Although these adverse events are believed to be related to the ergoline structure of these compounds, whether other, nonergot derived dopamine agonists can cause them is unknown.

A small number of reports have been received of possible fibrotic complications, including peritoneal fibrosis, pleural fibrosis, and pulmonary fibrosis in the post-marketing experience for Mirapex® (pramipexole dihydrochloride) tablets. While the evidence is not sufficient to establish a causal relationship between MIRAPEX tablets and these fibrotic complications, a contribution of MIRAPEX tablets cannot be completely ruled out in rare cases.

Melanoma

Epidemiological studies have shown that patients with Parkinson’s disease have a higher risk (2- to approximately 6-fold higher) of developing melanoma than the general population. Whether the increased risk observed was due to Parkinson’s disease or other factors, such as drugs used to treat Parkinson’s disease, is unclear.

For the reasons stated above, patients and providers are advised to monitor for melanomas frequently and on a regular basis when using MIRAPEX tablets for any indication. Ideally, periodic skin examinations should be performed by appropriately qualified individuals (e.g., dermatologists).

Impulse Control/Compulsive Behaviors

Cases of pathological gambling, hypersexuality, and compulsive eating (including binge eating), and compulsive shopping have been reported in patients treated with dopamine agonist therapy, including pramipexole therapy. As described in the literature, such behaviors are generally reversible upon dose reduction or treatment discontinuation.

Rebound and Augmentation in RLS

Reports in the literature indicate treatment of RLS with dopaminergic medications can result in a shifting of symptoms to the early morning hours, referred to as rebound. Rebound was not reported in the clinical trials of MIRAPEX tablets but the trials were generally not of sufficient duration to capture this phenomenon. Augmentation has also been described during therapy for RLS. Augmentation refers to the earlier onset of symptoms in the evening (or even the afternoon), increase in symptoms, and spread of symptoms to involve other extremities. In a controlled trial of MIRAPEX tablets for RLS, approximately 20% of both the Mirapex- and the placebo-treated patients reported at least a 2-hour earlier onset of symptoms during the day by the end of 3 months of treatment. The frequency and severity of augmentation and/or rebound after longer-term use of MIRAPEX tablets and the appropriate management of these events have not been adequately evaluated in controlled clinical trials.

Information for Patients (also see Patient Package Insert)

Patients should be instructed to take MIRAPEX tablets only as prescribed.

Patients should be alerted to the potential sedating effects associated with MIRAPEX tablets, including somnolence and the possibility of falling asleep while engaged in activities of daily living. Since somnolence is a frequent adverse event with potentially serious consequences, patients should neither drive a car nor engage in other potentially dangerous activities until they have gained sufficient experience with Mirapex® (pramipexole dihydrochloride) tablets to gauge whether or not it affects their mental and/or motor performance adversely. Patients should be advised that if increased somnolence or new episodes of falling asleep during activities of daily living (e.g., watching television, passenger in a car, etc.) are experienced at any time during treatment, they should not drive or participate in potentially dangerous activities until they have contacted their physician. Because of possible additive effects, caution should be advised when patients are taking other sedating medications or alcohol in combination with MIRAPEX tablets and when taking concomitant medications that increase plasma levels of pramipexole (e.g., cimetidine).

Patients should be informed that hallucinations can occur and that the elderly are at a higher risk than younger patients with Parkinson's disease. In clinical trials, patients with RLS treated with pramipexole rarely reported hallucinations.

There have been reports of patients experiencing intense urges to gamble, increased sexual urges and other intense urges and the inability to control these urges while taking one or more of the medications that increase central dopaminergic tone, that are generally used for the treatment of Parkinson’s disease, including MIRAPEX tablets. Although it is not proven that the medications caused these events, these urges were reported to have stopped in some cases when the dose was reduced or the medication was stopped. Prescribers should ask patients about the development of new or increased gambling urges, sexual urges, or other urges while being treated with MIRAPEX tablets. Patients should inform their physician if they experience new or increased gambling urges, increased sexual urges or other intense urges while taking MIRAPEX tablets. Physicians should consider dose reduction or stopping the medication if a patient develops such urges while taking MIRAPEX tablets.

Patients may develop postural (orthostatic) hypotension, with or without symptoms such as dizziness, nausea, fainting or blackouts, and sometimes, sweating. Hypotension may occur more frequently during initial therapy. Accordingly, patients should be cautioned against rising rapidly after sitting or lying down, especially if they have been doing so for prolonged periods and especially at the initiation of treatment with MIRAPEX tablets.

Because the teratogenic potential of pramipexole has not been completely established in laboratory animals, and because experience in humans is limited, patients should be advised to notify their physicians if they become pregnant or intend to become pregnant during therapy (see PRECAUTIONS, Pregnancy).

Because of the possibility that pramipexole may be excreted in breast milk, patients should be advised to notify their physicians if they intend to breast-feed or are breast-feeding an infant.

If patients develop nausea, they should be advised that taking MIRAPEX tablets with food may reduce the occurrence of nausea.

Laboratory Tests

During the development of MIRAPEX tablets, no systematic abnormalities on routine laboratory testing were noted. Therefore, no specific guidance is offered regarding routine monitoring; the practitioner retains responsibility for determining how best to monitor the patient in his or her care.

Drug Interactions

Carbidopa/levodopa: Carbidopa/levodopa did not influence the pharmacokinetics of pramipexole in healthy volunteers (N=10). Pramipexole did not alter the extent of absorption (AUC) or the elimination of carbidopa/levodopa, although it caused an increase in levodopa Cmax by about 40% and a decrease in Tmax from 2.5 to 0.5 hours.

Selegiline: In healthy volunteers (N=11), selegiline did not influence the pharmacokinetics of pramipexole.

Amantadine: Population pharmacokinetic analyses suggest that amantadine may slightly decrease the oral clearance of pramipexole.

Cimetidine: Cimetidine, a known inhibitor of renal tubular secretion of organic bases via the cationic transport system, caused a 50% increase in pramipexole AUC and a 40% increase in half-life (N=12).

Probenecid: Probenecid, a known inhibitor of renal tubular secretion of organic acids via the anionic transporter, did not noticeably influence pramipexole pharmacokinetics (N=12).

Other drugs eliminated via renal secretion: Population pharmacokinetic analysis suggests that coadministration of drugs that are secreted by the cationic transport system (e.g., cimetidine, ranitidine, diltiazem, triamterene, verapamil, quinidine, and quinine) decreases the oral clearance of pramipexole by about 20%, while those secreted by the anionic transport system (e.g., cephalosporins, penicillins, indomethacin, hydrochlorothiazide, and chlorpropamide) are likely to have little effect on the oral clearance of pramipexole.

CYP interactions: Inhibitors of cytochrome P450 enzymes would not be expected to affect pramipexole elimination because pramipexole is not appreciably metabolized by these enzymes in vivo or in vitro. Pramipexole does not inhibit CYP enzymes CYP1A2, CYP2C9, CYP2C19, CYP2E1, and CYP3A4. Inhibition of CYP2D6 was observed with an apparent Ki of 30 µM, indicating that pramipexole will not inhibit CYP enzymes at plasma concentrations observed following the clinical dose of 4.5 mg/day (1.5 mg TID).

Dopamine antagonists: Since pramipexole is a dopamine agonist, it is possible that dopamine antagonists, such as the neuroleptics (phenothiazines, butyrophenones, thioxanthenes) or metoclopramide, may diminish the effectiveness of Mirapex® (pramipexole dihydrochloride) tablets.

Drug/Laboratory Test Interactions

There are no known interactions between MIRAPEX tablets and laboratory tests.

Carcinogenesis, Mutagenesis, Impairment of Fertility

Two-year carcinogenicity studies with pramipexole have been conducted in mice and rats. Pramipexole was administered in the diet to Chbb:NMRI mice at doses of 0.3, 2, and 10 mg/kg/day [0.3, 2.2, and 11 times the Maximum Recommended Human Dose (MRHD) (MRHD of 1.5 mg TID on a mg/m^2 basis)]. Pramipexole was administered in the diet to Wistar rats at 0.3, 2, and 8 mg/kg/day (plasma AUCs were 0.3, 2.5, and 12.5 times the AUC in humans at the MRHD). No significant increases in tumors occurred in either species.

Pramipexole was not mutagenic or clastogenic in a battery of assays, including the in vitro Ames assay, V79 gene mutation assay for HGPRT mutants, chromosomal aberration assay in Chinese hamster ovary cells, and in vivo mouse micronucleus assay.

In rat fertility studies, pramipexole at a dose of 2.5 mg/kg/day (5 times the MRHD on a mg/m^2 basis), prolonged estrus cycles and inhibited implantation. These effects were associated with reductions in serum levels of prolactin, a hormone necessary for implantation and maintenance of early pregnancy in rats.

Pregnancy

Teratogenic Effect: Pregnancy Category C.

When pramipexole was given to female rats throughout pregnancy, implantation was inhibited at a dose of 2.5 mg/kg/day (5 times the MRHD on a mg/m^2 basis). Administration of 1.5 mg/kg/day of pramipexole to pregnant rats during the period of organogenesis (gestation days 7 through 16) resulted in a high incidence of total resorption of embryos. The plasma AUC in rats at this dose was 4 times the AUC in humans at the MRHD. These findings are thought to be due to the prolactin-lowering effect of pramipexole, since prolactin is necessary for implantation and maintenance of early pregnancy in rats (but not rabbits or humans). Because of pregnancy disruption and early embryonic loss in these studies, the teratogenic potential of pramipexole could not be adequately evaluated. There was no evidence of adverse effects on embryo-fetal development following administration of up to 10 mg/kg/day to pregnant rabbits during organogenesis (plasma AUC was 71 times that in humans at the MRHD). Postnatal growth was inhibited in the offspring of rats treated with 0.5 mg/kg/day (approximately equivalent to the MRHD on a mg/m^2 basis) or greater during the latter part of pregnancy and throughout lactation.

There are no studies of pramipexole in human pregnancy. Because animal reproduction studies are not always predictive of human response, pramipexole should be used during pregnancy only if the potential benefit outweighs the potential risk to the fetus.

Nursing Mothers

A single-dose, radio-labeled study showed that drug-related materials were excreted into the breast milk of lactating rats. Concentrations of radioactivity in milk were three to six times higher than concentrations in plasma at equivalent time points.

Other studies have shown that pramipexole treatment resulted in an inhibition of prolactin secretion in humans and rats.

It is not known whether this drug is excreted in human milk. Because many drugs are excreted in human milk and because of the potential for serious adverse reactions in nursing infants from pramipexole, a decision should be made as to whether to discontinue nursing or to discontinue the drug, taking into account the importance of the drug to the mother.

Pediatric Use

The safety and efficacy of Mirapex® (pramipexole dihydrochloride) tablets in pediatric patients has not been established.

Geriatric Use

Pramipexole total oral clearance was approximately 30% lower in subjects older than 65 years compared with younger subjects, because of a decline in pramipexole renal clearance due to an age-related reduction in renal function. This resulted in an increase in elimination half-life from approximately 8.5 hours to 12 hours. In clinical studies with Parkinson’s disease patients, 38.7% of patients were older than 65 years. There were no apparent differences in efficacy or safety between older and younger patients, except that the relative risk of hallucination associated with the use of MIRAPEX tablets was increased in the elderly. In clinical studies with RLS patients, 22% of patients were at least 65 years old. There were no apparent differences in efficacy or safety between older and younger patients.

ADVERSE EVENTS

Parkinson's Disease

During the premarketing development of pramipexole, patients with either early or advanced Parkinson's disease were enrolled in clinical trials. Apart from the severity and duration of their disease, the two populations differed in their use of concomitant levodopa therapy. Patients with early disease did not receive concomitant levodopa therapy during treatment with pramipexole; those with advanced Parkinson's disease all received concomitant levodopa treatment. Because these two populations may have differential risks for various adverse events, this section will, in general, present adverse-event data for these two populations separately.

Because the controlled trials performed during premarketing development all used a titration design, with a resultant confounding of time and dose, it was impossible to adequately evaluate the effects of dose on the incidence of adverse events.

Early Parkinson's Disease

In the three double-blind, placebo-controlled trials of patients with early Parkinson's disease, the most commonly observed adverse events (>5%) that were numerically more frequent in the group treated with MIRAPEX tablets were nausea, dizziness, somnolence, insomnia, constipation, asthenia, and hallucinations.

Approximately 12% of 388 patients with early Parkinson's disease and treated with MIRAPEX tablets who participated in the double-blind, placebo-controlled trials discontinued treatment due to adverse events compared with 11% of 235 patients who received placebo. The adverse events most commonly causing discontinuation of treatment were related to the nervous system (hallucinations [3.1% on MIRAPEX tablets vs 0.4% on placebo]; dizziness [2.1% on MIRAPEX tablets vs 1% on placebo]; somnolence [1.6% on MIRAPEX tablets vs 0% on placebo]; extrapyramidal syndrome [1.6% on MIRAPEX tablets vs 6.4% on placebo]; headache and confusion [1.3% and 1.0%, respectively, on Mirapex® (pramipexole dihydrochloride) tablets vs 0% on placebo]); and gastrointestinal system (nausea [2.1% on MIRAPEX tablets vs 0.4% on placebo]).

Adverse-event Incidence in Controlled Clinical Studies in Early Parkinson's Disease

Table 3 lists treatment-emergent adverse events that occurred in the double-blind, placebo-controlled studies in early Parkinson's disease that were reported by ≥1% of patients treated with MIRAPEX tablets and were numerically more frequent than in the placebo group. In these studies, patients did not receive concomitant levodopa. Adverse events were usually mild or moderate in intensity.

The prescriber should be aware that these figures cannot be used to predict the incidence of adverse events in the course of usual medical practice where patient characteristics and other factors differ from those that prevailed in the clinical studies. Similarly, the cited frequencies cannot be compared with figures obtained from other clinical investigations involving different treatments, uses, and investigators. However, the cited figures do provide the prescribing physician with some basis for estimating the relative contribution of drug and nondrug factors to the adverse-event incidence rate in the population studied.

Table 3 Treatment-Emergent Adverse-Event* Incidence in Double-Blind, Placebo-Controlled Trials in Early Parkinson's Disease (Events ≥1% of Patients Treated with MIRAPEX tablets and Numerically More Frequent than in the Placebo Group)
Body System/ Adverse Event | MIRAPEX N=388 | Placebo N=235
Body as a Whole
Asthenia | 14 | 12
General edema | 5 | 3
Malaise | 2 | 1
Reaction unevaluable | 2 | 1
Fever | 1 | 0
Digestive System
Nausea | 28 | 18
Constipation | 14 | 6
Anorexia | 4 | 2
Dysphagia | 2 | 0
Metabolic & Nutritional System
Peripheral edema | 5 | 4
Decreased weight | 2 | 0
Nervous System
Dizziness | 25 | 24
Somnolence | 22 | 9
Insomnia | 17 | 12
Hallucinations | 9 | 3
Confusion | 4 | 1
Amnesia | 4 | 2
Hypesthesia | 3 | 1
Dystonia | 2 | 1
Akathisia | 2 | 0
Thinking abnormalities | 2 | 0
Decreased libido | 1 | 0
Myoclonus | 1 | 0
Special Senses
Vision abnormalities | 3 | 0
Urogenital System
Impotence | 2 | 1
*Patients may have reported multiple adverse experiences during the study or at discontinuation; thus, patients may be included in more than one category.

Other events reported by 1% or more of patients with early Parkinson's disease and treated with Mirapex® (pramipexole dihydrochloride) tablets but reported equally or more frequently in the placebo group were infection, accidental injury, headache, pain, tremor, back pain, syncope, postural hypotension, hypertonia, depression, abdominal pain, anxiety, dyspepsia, flatulence, diarrhea, rash, ataxia, dry mouth, extrapyramidal syndrome, leg cramps, twitching, pharyngitis, sinusitis, sweating, rhinitis, urinary tract infection, vasodilation, flu syndrome, increased saliva, tooth disease, dyspnea, increased cough, gait abnormalities, urinary frequency, vomiting, allergic reaction, hypertension, pruritis, hypokinesia, increased creatine PK, nervousness, dream abnormalities, chest pain, neck pain, paresthesia, tachycardia, vertigo, voice alteration, conjunctivitis, paralysis, accommodation abnormalities, tinnitus, diplopia, and taste perversions.

In a fixed-dose study in early Parkinson's disease, occurrence of the following events increased in frequency as the dose increased over the range from 1.5 mg/day to 6 mg/day: postural hypotension, nausea, constipation, somnolence, and amnesia. The frequency of these events was generally 2-fold greater than placebo for pramipexole doses greater than 3 mg/day. The incidence of somnolence with pramipexole at a dose of 1.5 mg/day was comparable to that reported for placebo.

Advanced Parkinson's Disease

In the four double-blind, placebo-controlled trials of patients with advanced Parkinson's disease, the most commonly observed adverse events (>5%) that were numerically more frequent in the group treated with MIRAPEX tablets and concomitant levodopa were postural (orthostatic) hypotension, dyskinesia, extrapyramidal syndrome, insomnia, dizziness, hallucinations, accidental injury, dream abnormalities, confusion, constipation, asthenia, somnolence, dystonia, gait abnormality, hypertonia, dry mouth, amnesia, and urinary frequency.

Approximately 12% of 260 patients with advanced Parkinson's disease who received Mirapex® (pramipexole dihydrochloride) tablets and concomitant levodopa in the double-blind, placebo-controlled trials discontinued treatment due to adverse events compared with 16% of 264 patients who received placebo and concomitant levodopa. The events most commonly causing discontinuation of treatment were related to the nervous system (hallucinations [2.7% on MIRAPEX tablets vs 0.4% on placebo]; dyskinesia [1.9% on MIRAPEX tablets vs 0.8% on placebo]; extrapyramidal syndrome [1.5% on MIRAPEX tablets vs 4.9% on placebo]; dizziness [1.2% on MIRAPEX tablets vs 1.5% on placebo]; confusion [1.2% on MIRAPEX tablets vs 2.3% on placebo]); and cardiovascular system (postural [orthostatic] hypotension [2.3% on MIRAPEX tablets vs 1.1% on placebo]).

Adverse-event Incidence in Controlled Clinical Studies in Advanced Parkinson's Disease

Table 4 lists treatment-emergent adverse events that occurred in the double-blind, placebo-controlled studies in advanced Parkinson's disease that were reported by ≥1% of patients treated with MIRAPEX tablets and were numerically more frequent than in the placebo group. In these studies, MIRAPEX tablets or placebo was administered to patients who were also receiving concomitant levodopa. Adverse events were usually mild or moderate in intensity.

The prescriber should be aware that these figures cannot be used to predict the incidence of adverse events in the course of usual medical practice where patient characteristics and other factors differ from those that prevailed in the clinical studies. Similarly, the cited frequencies cannot be compared with figures obtained from other clinical investigations involving different treatments, uses, and investigators. However, the cited figures do provide the prescribing physician with some basis for estimating the relative contribution of drug and nondrug factors to the adverse-events incidence rate in the population studied.

Table 4 Treatment-Emergent Adverse-Event* Incidence in Double-Blind, Placebo-Controlled Trials in Advanced Parkinson's Disease (Events ≥1% of Patients Treated with MIRAPEX tablets and Numerically More Frequent than in the Placebo Group)
Body System/ Adverse Event | MIRAPEX† (pramipexole dihydrochloride) N=260 | Placebo† N=264
Body as a Whole
Accidental injury | 17 | 15
Asthenia | 10 | 8
General edema | 4 | 3
Chest pain | 3 | 2
Malaise | 3 | 2
Cardiovascular System
Postural hypotension | 53 | 48
Digestive System
Constipation | 10 | 9
Dry mouth | 7 | 3
Metabolic & Nutritional System
Peripheral edema | 2 | 1
Increased creatine PK | 1 | 0
Musculoskeletal System
Arthritis | 3 | 1
Twitching | 2 | 0
Bursitis | 2 | 0
Myasthenia | 1 | 0
Nervous System
Dyskinesia | 47 | 31
Extrapyramidal syndrome | 28 | 26
Insomnia | 27 | 22
Dizziness | 26 | 25
Hallucinations | 17 | 4
Dream abnormalities | 11 | 10
Confusion | 10 | 7
Somnolence | 9 | 6
Dystonia | 8 | 7
Gait abnormalities | 7 | 5
Hypertonia | 7 | 6
Amnesia | 6 | 4
Akathisia | 3 | 2
Thinking abnormalities | 3 | 2
Paranoid reaction | 2 | 0
Delusions | 1 | 0
Sleep disorders | 1 | 0
Respiratory System
Dyspnea | 4 | 3
Rhinitis | 3 | 1
Pneumonia | 2 | 0
Skin & Appendages
Skin disorders | 2 | 1
Special Senses
Accommodation abnormalities | 4 | 2
Vision abnormalities | 3 | 1
Diplopia | 1 | 0
Urogenital System
Urinary frequency | 6 | 3
Urinary tract infection | 4 | 3
Urinary incontinence | 2 | 1
* Patients may have reported multiple adverse experiences during the study or at discontinuation; thus, patients may be included in more than one category.
† Patients received concomitant levodopa.

Other events reported by 1% or more of patients with advanced Parkinson's disease and treated with Mirapex® (pramipexole dihydrochloride) tablets but reported equally or more frequently in the placebo group were nausea, pain, infection, headache, depression, tremor, hypokinesia, anorexia, back pain, dyspepsia, flatulence, ataxia, flu syndrome, sinusitis, diarrhea, myalgia, abdominal pain, anxiety, rash, paresthesia, hypertension, increased saliva, tooth disorder, apathy, hypotension, sweating, vasodilation, vomiting, increased cough, nervousness, pruritus, hypesthesia, neck pain, syncope, arthralgia, dysphagia, palpitations, pharyngitis, vertigo, leg cramps, conjunctivitis, and lacrimation disorders.

Restless Legs Syndrome

MIRAPEX tablets for treatment of RLS have been evaluated for safety in 889 patients, including 427 treated for over six months and 75 for over one year.

The overall safety assessment focuses on the results of three double-blind, placebo-controlled trials, in which 575 patients with RLS were treated with MIRAPEX tablets for up to 12 weeks. The most commonly observed adverse events with MIRAPEX tablets in the treatment of RLS (observed in > 5% of pramipexole-treated patients and at a rate at least twice that observed in placebo-treated patients) were nausea and somnolence. Occurrences of nausea and somnolence in clinical trials were generally mild and transient.

Approximately 7% of 575 patients treated with MIRAPEX tablets during the double-blind periods of three placebo-controlled trials discontinued treatment due to adverse events compared to 5% of 223 patients who received placebo. The adverse event most commonly causing discontinuation of treatment was nausea (1%).

Table 5 lists treatment-emergent events that occurred in three double-blind, placebo-controlled studies in RLS patients that were reported by ≥ 2% of patients treated with MIRAPEX tablets and were numerically more frequent than in the placebo group.

The prescriber should be aware that these figures cannot be used to predict the incidence of adverse events in the course of usual medical practice where patient characteristics and other factors differ from those that prevailed in the clinical studies. Similarly, the cited frequencies cannot be compared with figures obtained from other clinical investigations involving different treatments, uses, and investigators. However, the cited figures do provide the prescribing physician with some basis for estimating the relative contribution of drug and nondrug factors to the adverse-event incidence rate in the population studied.

Table 5 Treatment-Emergent Adverse-Event* Incidence in Double-Blind, Placebo-Controlled Trials in Restless Legs Syndrome (Events ≥ 2% of Patients Treated with MIRAPEX tablets and Numerically More Frequent than in the Placebo Group)
Body System/ Adverse Event | MIRAPEX 0.125 – 0.75 mg/day (N=575) % | Placebo (N=223) %
Gastrointestinal disorders
Nausea | 16 | 5
Constipation | 4 | 1
Diarrhea | 3 | 1
Dry mouth | 3 | 1
General disorders and administration site conditions
Fatigue | 9 | 7
Infections and infestations
Influenza | 3 | 1
Nervous system disorders
Headache | 16 | 15
Somnolence | 6 | 3
*Patients may have reported multiple adverse experiences during the study or at discontinuation; thus, patients may be included in more than one category.

Other events reported by 2% or more of RLS patients treated with Mirapex® (pramipexole dihydrochloride) tablets but equally or more frequently in the placebo group, were: vomiting, nasopharyngitis, back pain, pain in extremity, dizziness, and insomnia.

Table 6 summarizes data for adverse events that appeared to be dose related in the 12-week fixed dose study.

Table 6 Dose Related Adverse Events in a 12-Week Double-Blind, Placebo-Controlled Fixed Dose Study in Restless Legs Syndrome (Occurring in ≥5% of all Patients in the Treatment Phase)
Body System/ Adverse Event | MIRAPEX 0.25 mg (N=88) % | MIRAPEX 0.5 mg (N=80) % | MIRAPEX 0.75 mg (N=90) % | Placebo (n=86) %
Gastrointestinal disorders
Nausea | 11 | 19 | 27 | 5
Diarrhea | 3 | 1 | 7 | 0
Dyspepsia | 3 | 1 | 4 | 7
Infections and infestations
Influenza | 1 | 4 | 7 | 1
General disorders and administration site conditions
Fatigue | 3 | 5 | 7 | 5
Psychiatric disorders
Insomnia | 9 | 9 | 13 | 9
Abnormal dreams | 2 | 1 | 8 | 2
Respiratory, thoracic and mediastinal disorders
Nasal congestion | 0 | 3 | 6 | 1
Musculoskeletal and connective tissue disorders
Pain in extremity | 3 | 3 | 7 | 1

General

Adverse Events; Relationship to Age, Gender, and Race

Among the treatment-emergent adverse events in patients treated with MIRAPEX tablets, hallucination appeared to exhibit a positive relationship to age in patients with Parkinson’s disease. Although no gender-related differences were observed in Parkinson’s disease patients, nausea and fatigue, both generally transient, were more frequently reported by female than male RLS patients. Less than 4% of patients enrolled were non-Caucasian, therefore, an evaluation of adverse events related to race is not possible.

Other Adverse Events Observed During Phase 2 and 3 Clinical Trials

MIRAPEX tablets have been administered to 1620 Parkinson’s disease patients and to 889 RLS patients in Phase 2 and 3 clinical trials. During these trials, all adverse events were recorded by the clinical investigators using terminology of their own choosing; similar types of events were grouped into a smaller number of standardized categories using MedDRA dictionary terminology. These categories are used in the listing below. Adverse events which are not listed above but occurred on at least two occasions (one occasion if the event was serious) in the 2509 individuals exposed to MIRAPEX tablets are listed below. The reported events below are included without regard to determination of a causal relationship to MIRAPEX tablets.

Blood and lymphatic system disorders: anemia, iron deficiency anemia, leukocytosis, leukopenia, lymphadenitis, lymphadenopathy, thrombocythaemia, thrombocytopenia

Cardiac disorders: angina pectoris, arrhythmia supraventricular, atrial fibrillation, atrioventricular block first degree, atrioventricular block second degree, bradycardia, bundle branch block, cardiac arrest, cardiac failure, cardiac failure congestive, cardiomegaly, coronary artery occlusion, cyanosis, extrasystoles, left ventricular failure, myocardial infarction, nodal arrhythmia, sinus arrhythmia, sinus bradycardia, sinus tachycardia, supraventricular extrasystoles, supraventricular tachycardia, tachycardia, ventricular fibrillation, ventricular extrasystoles, ventricular hypertrophy

Congenital, familial and genetic disorders: atrial septal defect, congenital foot malformation, spine malformation

Ear and labyrinth disorders: deafness, ear pain, hearing impaired, hypoacusis, motion sickness, vestibular ataxia

Endocrine disorders: goiter, hyperthyroidism, hypothyroidism

Eye disorders: amaurosis fugax, blepharitis, blepharospasm, cataract, dacryostenosis acquired, dry eye, eye hemorrhage, eye irritation, eye pain, eyelid edema, eyelid ptosis, glaucoma, keratitis, macular degeneration, myopia, photophobia, retinal detachment, retinal vascular disorder, scotoma, vision blurred, visual acuity reduced, vitreous floaters

Gastrointestinal disorders: abdominal discomfort, abdominal distension, aphthous stomatitis, ascites, cheilitis, colitis, colitis ulcerative, duodenal ulcer, duodenal ulcer hemorrhage, enteritis, eructation, fecal incontinence, gastric ulcer, gastric ulcer hemorrhage, gastritis, gastrointestinal hemorrhage, gastroesophageal reflux disease, gingivitis, haematemesis, haematochezia, hemorrhoids, hiatus hernia, hyperchlorhydria, ileus, inguinal hernia, intestinal obstruction, irritable bowel syndrome, esophageal spasm, esophageal stenosis, esophagitis, pancreatitis, periodontitis, rectal hemorrhage, reflux esophagitis, tongue edema, tongue ulceration, toothache, umbilical hernia

General disorders: chest discomfort, chills, death, drug withdrawal syndrome, face edema, feeling cold, feeling hot, feeling jittery, gait disturbance, impaired healing, influenza-like illness, irritability, localized edema, edema, pitting edema, thirst

Hepatobiliary disorders: biliary colic, cholecystitis, cholecystitis chronic, cholelithiasis

Immune system disorders: drug hypersensitivity

Infections and infestations: abscess, acute tonsillitis, appendicitis, bronchiolitis, bronchitis, bronchopneumonia, cellulitis, cystitis, dental caries, diverticulitis, ear infection, eye infection, folliculitis, fungal infection, furuncle, gangrene, gastroenteritis, gingival infection, herpes simplex, herpes zoster, hordeolum, intervertebral discitis, laryngitis, lobar pneumonia, nail infection, onychomycosis, oral candidiasis, orchitis, osteomyelitis, otitis externa, otitis media, paronychia, pyelonephritis, pyoderma, sepsis, skin infection, tonsillitis, tooth abscess, tooth infection, upper respiratory tract infection, urethritis, vaginal candidiasis, vaginal infection, viral infection, wound infection

Injury, poisoning and procedural complications: accidental falls, drug toxicity epicondylitis, road traffic accident, sunburn, tendon rupture

Metabolism and nutrition disorders: cachexia, decreased appetite, dehydration, diabetes mellitus, fluid retention, gout, hypercholesterolemia, hyperglycemia, hyperlipidemia, hyperuricemia, hypocalcemia, hypoglycemia, hypokalemia, hyponatremia, hypovitaminosis, increased appetite, metabolic alkalosis

Musculoskeletal and connective tissue disorders: bone pain, fasciitis, flank pain, intervertebral disc disorder, intervertebral disc protrusion, joint effusion, joint stiffness, joint swelling, monarthritis, muscle rigidity, muscle spasms, musculoskeletal stiffness, myopathy, myositis, nuchal rigidity, osteoarthritis, osteonecrosis, osteoporosis, polymyalgia, rheumatoid arthritis, shoulder pain, spinal osteoarthritis, tendonitis, tenosynovitis

Neoplasms benign, malignant and unspecified: abdominal neoplasm, adenocarcinoma, adenoma benign, basal cell carcinoma, bladder cancer, breast cancer, breast neoplasm, chronic lymphocytic leukemia, colon cancer, colorectal cancer, endometrial cancer, gallbladder cancer, gastric cancer, gastrointestinal neoplasm, hemangioma, hepatic neoplasm, hepatic neoplasm malignant, lip and/or oral cavity cancer, lung neoplasm malignant, lung cancer metastatic, lymphoma, malignant melanoma, melanocytic naevus, metastases to lung, multiple myeloma, oral neoplasm benign, neoplasm, neoplasm malignant, neoplasm prostate, neoplasm skin, neuroma, ovarian cancer, prostate cancer, prostatic adenoma, pseudo lymphoma, renal neoplasm, skin cancer, skin papilloma, squamous cell carcinoma, thyroid neoplasm, uterine leiomyoma

Nervous system disorders: ageusia, akinesia, anticholinergic syndrome, aphasia, balance disorder, brain edema, carotid artery occlusion, carpal tunnel syndrome, cerebral artery embolism, cerebral hemorrhage, cerebral infarction, cerebral ischemia, chorea, cognitive disorder, coma, convulsion, coordination abnormal, dementia, depressed level of consciousness, disturbance in attention, dizziness postural, dysarthria, dysgraphia, facial palsy, grand mal convulsion, hemiplegia, hyperaesthesia, hyperkinesia, hyperreflexia, hyporeflexia, hypotonia, lethargy, loss of consciousness, memory impairment, migraine, muscle contractions involuntary, narcolepsy, neuralgia, neuropathy, nystagmus, parosmia, psychomotor hyperactivity, sciatica, sedation, sensory disturbance, sleep phase rhythm disturbance, sleep talking, stupor, syncope vasovagal, tension headache

Psychiatric disorders: affect lability, aggression, agitation, bradyphrenia, bruxism, suicide, delirium, delusional disorder persecutory type, disorientation, dissociation, emotional distress, euphoric mood, hallucination auditory, hallucination visual, initial insomnia, libido increased, mania, middle insomnia, mood altered, nightmare, obsessive thoughts, obsessive-compulsive disorder, panic reaction, parasomnia, personality disorder, psychotic disorder, restlessness, sleep walking, suicidal ideation

Renal and urinary disorders: chromaturia, dysuria, glycosuria, hematuria, urgency, nephrolithiasis, neurogenic bladder, nocturia, oliguria, pollakiuria, proteinuria, renal artery stenosis, renal colic, renal cyst, renal failure, renal impairment, urinary retention

Reproductive system and breast disorders: amenorrhea, breast pain, dysmenorrhea, epididymitis, gynaecomastia, menopausal symptoms, menorrhagia, metrorrhagia, ovarian cyst, priapism, prostatitis, sexual dysfunction, uterine hemorrhage, vaginal discharge, vaginal hemorrhage

Respiratory, thoracic and mediastinal disorders: apnea, aspiration, asthma, choking, chronic obstructive pulmonary disease, dry throat, dysphonia, dyspnea exertional, epistaxis, haemoptysis, hiccups, hyperventilation, increased bronchial secretion, laryngospasm, nasal dryness, nasal polyps, obstructive airways disorder, pharyngolaryngeal pain, pleurisy, pneumonia aspiration, pneumothorax, postnasal drip, productive cough, pulmonary embolism, pulmonary edema, respiratory alkalosis, respiratory distress, respiratory failure, respiratory tract congestion, rhinitis allergic, rhinorrhea, sinus congestion, sleep apnoea syndrome, sneezing, snoring, tachypnea, wheezing

Skin and subcutaneous tissue disorders: acne, alopecia, cold sweat, dermal cyst, dermatitis, dermatitis bullous, dermatitis contact, dry skin, ecchymosis, eczema, erythema, hyperkeratosis, livedo reticularis, night sweats, periorbital edema, petechiae, photosensitivity allergic reaction, psoriasis, purpura, rash erythematous, rash maculo-papular, rash papular, rosacea, seborrhea, seborrheic dermatitis, skin burning sensation, skin discoloration, skin exfoliation, skin hyperpigmentation, skin hypertrophy, skin irritation, skin nodule, skin odor abnormal, skin ulcer, urticaria

Vascular disorders: aneurysm, angiopathy, arteriosclerosis, circulatory collapse, deep vein thrombosis, embolism, hematoma, hot flush, hypertensive crisis, lymphoedema, pallor, phlebitis, Raynaud’s phenomenon, shock, thrombophlebitis, thrombosis, varicose vein

Falling Asleep During Activities of Daily Living

Patients treated with Mirapex® (pramipexole dihydrochloride) tablets have reported falling asleep while engaged in activities of daily living, including operation of a motor vehicle which sometimes resulted in accidents (see bolded WARNING).

Post-Marketing Experience

In addition to the adverse events reported during clinical trials, the following adverse reactions have been identified during post-approval use of MIRAPEX tablets, primarily in Parkinson’s disease patients. Because these reactions are reported voluntarily from a population of uncertain size, it is not always possible to reliably estimate their frequency or establish a causal relationship to drug exposure. Decisions to include these reactions in labeling are typically based on one or more of the following factors: (1) seriousness of the reaction, (2) frequency of reporting, or (3) strength of causal connection to pramipexole tablets. Similar types of events were grouped into a smaller number of standardized categories using the MedDRA dictionary: abnormal behavior, abnormal dreams, accidents (including fall), blackouts, compulsive shopping, fatigue, hallucinations (all kinds), headache, hypotension (including postural hypotension), increased eating (including binge eating, compulsive eating, and hyperphagia), libido disorders (including increased and decreased libido, and hypersexuality), pathological gambling, pruritus, syncope, vomiting, and weight increase.

DRUG ABUSE AND DEPENDENCE

Pramipexole is not a controlled substance. Pramipexole has not been systematically studied in animals or humans for its potential for abuse, tolerance, or physical dependence. However, in a rat model on cocaine self-administration, pramipexole had little or no effect.

OVERDOSAGE

There is no clinical experience with massive overdosage. One patient, with a 10-year history of schizophrenia, took 11 mg/day of pramipexole for 2 days in a clinical trial to evaluate the effect of pramipexole in schizophrenic patients. No adverse events were reported related to the increased dose. Blood pressure remained stable although pulse rate increased to between 100 and 120 beats/minute. The patient withdrew from the study at the end of week 2 due to lack of efficacy.

There is no known antidote for overdosage of a dopamine agonist. If signs of central nervous system stimulation are present, a phenothiazine or other butyrophenone neuroleptic agent may be indicated; the efficacy of such drugs in reversing the effects of overdosage has not been assessed. Management of overdose may require general supportive measures along with gastric lavage, intravenous fluids, and electrocardiogram monitoring.

DOSAGE AND ADMINISTRATION

Parkinson's Disease

In all clinical studies, dosage was initiated at a subtherapeutic level to avoid intolerable adverse effects and orthostatic hypotension. Mirapex® (pramipexole dihydrochloride) tablets should be titrated gradually in all patients. The dosage should be increased to achieve a maximum therapeutic effect, balanced against the principal side effects of dyskinesia, hallucinations, somnolence, and dry mouth.

Dosing in Patients with Normal Renal Function

Initial Treatment

Dosages should be increased gradually from a starting dose of 0.375 mg/day given in three divided doses and should not be increased more frequently than every 5 to 7 days. A suggested ascending dosage schedule that was used in clinical studies is shown in the following table:

Table 7 Ascending Dosage Schedule of MIRAPEX tablets for Parkinson's Disease
Week | Dosage (mg) | Total Daily Dose (mg)
1 | 0.125 TID | 0.375
2 | 0.25 TID | 0.75
3 | 0.5 TID | 1.50
4 | 0.75 TID | 2.25
5 | 1 TID | 3.0
6 | 1.25 TID | 3.75
7 | 1.5 TID | 4.50

Maintenance Treatment

Mirapex® (pramipexole dihydrochloride) tablets were effective and well tolerated over a dosage range of 1.5 to 4.5 mg/day administered in equally divided doses three times per day with or without concomitant levodopa (approximately 800 mg/day).

In a fixed-dose study in early Parkinson's disease patients, doses of 3 mg, 4.5 mg, and 6 mg per day of MIRAPEX tablets were not shown to provide any significant benefit beyond that achieved at a daily dose of 1.5 mg/day. However, in the same fixed-dose study, the following adverse events were dose related: postural hypotension, nausea, constipation, somnolence, and amnesia. The frequency of these events was generally 2-fold greater than placebo for pramipexole doses greater than 3 mg/day. The incidence of somnolence reported with pramipexole at a dose of 1.5 mg/day was comparable to placebo.

When MIRAPEX tablets are used in combination with levodopa, a reduction of the levodopa dosage should be considered. In a controlled study in advanced Parkinson's disease, the dosage of levodopa was reduced by an average of 27% from baseline.

Dosing in Patients with Renal Impairment

Table 8 Pramipexole Dosage in Parkinson’s Disease Patients with Renal Impairment
Renal Status | Starting Dose (mg) | Maximum Dose (mg)
Normal to mild impairment (creatinine Cl > 60 mL/min) | 0.125 TID | 1.5 TID
Moderate impairment (creatinine Cl = 35 to 59 mL/min) | 0.125 BID | 1.5 BID
Severe impairment (creatinine Cl = 15 to 34 mL/min) | 0.125 QD | 1.5 QD
Very severe impairment (creatinine Cl < 15 mL/min and hemodialysis patients) | The use of MIRAPEX tablets has not been adequately studied in this group of patients.

Discontinuation of Treatment

It is recommended that MIRAPEX tablets be discontinued over a period of 1 week; in some studies, however, abrupt discontinuation was uneventful.

Restless Legs Syndrome

The recommended starting dose of MIRAPEX tablets is 0.125 mg taken once daily 2-3 hours before bedtime. For patients requiring additional symptomatic relief, the dose may be increased every 4-7 days (Table 9). Although the dose of MIRAPEX tablets was increased to 0.75 mg in some patients during long-term open-label treatment, there is no evidence that the 0.75 mg dose provides additional benefit beyond the 0.5 mg dose.

Table 9 Ascending Dosage Schedule of MIRAPEX tablets for RLS
Titration Step | Duration | Dosage (mg) to be taken once daily, 2-3 hours before bedtime
1 | 4-7 days | 0.125
2* | 4-7 days | 0.25
3* | 4-7 days | 0.5
*if needed

Patients with Renal Impairment

The duration between titration steps should be increased to 14 days in RLS patients with severe and moderate renal impairment (creatinine clearance 20-60 mL/min) (see CLINICAL PHARMACOLOGY , Renal Insufficiency).

Discontinuation of Treatment

In clinical trials of patients being treated for RLS with doses up to 0.75 mg once daily, Mirapex® (pramipexole dihydrochloride) tablets were discontinued without a taper.

HOW SUPPLIED

MIRAPEX tablets are available as follows:

0.5 mg: white, oval, scored tablet with "BI BI" on one side and "85 85" on the reverse side.
Bottles of 90 NDC 21695-867-90

STORAGE AND HANDLING

Store at 25°C (77°F); excursions permitted to 15°-30°C (59°-86°F) [see USP Controlled Room Temperature]. Protect from light.

Store in a safe place out of the reach of children.

Address medical inquiries to: http://us.boehringer-ingelheim.com, (800) 542-6257 or (800) 459-9906 TTY.

ANIMAL TOXICOLOGY

Retinal Pathology in Albino Rats

Pathologic changes (degeneration and loss of photoreceptor cells) were observed in the retina of albino rats in the 2-year carcinogenicity study with pramipexole. These findings were first observed during week 76 and were dose dependent in animals receiving 2 or 8 mg/kg/day (plasma AUCs equal to 2.5 and 12.5 times the AUC in humans that received 1.5 mg TID). In a similar study of pigmented rats with 2 years exposure to pramipexole at 2 or 8 mg/kg/day, retinal degeneration was not diagnosed. Animals given drug had thinning in the outer nuclear layer of the retina that was only slightly greater than that seen in control rats utilizing morphometry.

Investigative studies demonstrated that pramipexole reduced the rate of disk shedding from the photoreceptor rod cells of the retina in albino rats, which was associated with enhanced sensitivity to the damaging effects of light. In a comparative study, degeneration and loss of photoreceptor cells occurred in albino rats after 13 weeks of treatment with 25 mg/kg/day of pramipexole (54 times the highest clinical dose on a mg/m^2 basis) and constant light (100 lux) but not in pigmented rats exposed to the same dose and higher light intensities (500 lux). Thus, the retina of albino rats is considered to be uniquely sensitive to the damaging effects of pramipexole and light. Similar changes in the retina did not occur in a 2-year carcinogenicity study in albino mice treated with 0.3, 2, or 10 mg/kg/day (0.3, 2.2 and 11 times the highest clinical dose on a mg/m^2 basis). Evaluation of the retinas of monkeys given 0.1, 0.5, or 2.0 mg/kg/day of pramipexole (0.4, 2.2, and 8.6 times the highest clinical dose on a mg/m^2 basis) for 12 months and minipigs given 0.3, 1, or 5 mg/kg/day of pramipexole for 13 weeks also detected no changes.

The potential significance of this effect in humans has not been established, but cannot be disregarded because disruption of a mechanism that is universally present in vertebrates (i.e., disk shedding) may be involved.

Fibro-osseous Proliferative Lesions in Mice

An increased incidence of fibro-osseous proliferative lesions occurred in the femurs of female mice treated for 2 years with 0.3, 2.0, or 10 mg/kg/day (0.3, 2.2, and 11 times the highest clinical dose on a mg/m^2 basis). Lesions occurred at a lower rate in control animals. Similar lesions were not observed in male mice or rats and monkeys of either sex that were treated chronically with pramipexole. The significance of this lesion to humans is not known.

Distributed by:
Boehringer Ingelheim Pharmaceuticals, Inc.
Ridgefield, CT 06877 USA

Licensed from:
Boehringer Ingelheim International GmbH

Trademark under license from:
Boehringer Ingelheim International GmbH

U.S. Patent Nos. 4,886,812; 6,001,861; and 6,194,445.

©2009, Boehringer Ingelheim International GmbH
ALL RIGHTS RESERVED

Rev: April 2009

OT1317PC2409
2001/05

OT1338H
10003128/08

IT1322G
10003129/07

PATIENT INFORMATION

Mirapex®
(pramipexole dihydrochloride)
0.125 mg, 0.25 mg, 0.5 mg, 0.75 mg,
1 mg, and 1.5 mg Tablets

Patient Information

Mirapex® [mîr′-ah-pěx] (pramipexole dihydrochloride) tablets

Read the Patient Information that comes with MIRAPEX before you start taking it and each time you get a refill. There may be some new information. This leaflet does not take the place of talking with your doctor about your medical condition or your treatment.

What is the most important information I should know about MIRAPEX?

MIRAPEX may cause you to fall asleep while you are doing daily activities such as driving, talking with other people, watching TV, or eating.

- Some people taking MIRAPEX have had car accidents because they fell asleep while driving.
- Some patients did not feel sleepy before they fell asleep while driving. You could fall asleep without any warning.

Do not drive a car, operate a machine, or do anything that needs you to be alert until you know how MIRAPEX affects you.

Tell your doctor right away if you fall asleep while you are doing activities such as talking with people, watching TV, eating, or driving, or if you feel sleepier than is normal for you.

What is MIRAPEX?

MIRAPEX is a prescription medicine to treat

- primary Restless Legs Syndrome.
- signs and symptoms of Parkinson's disease.

MIRAPEX has not been studied in children.

Who should not take MIRAPEX?

Do not take MIRAPEX if you are allergic to pramipexole or any of the inactive ingredients of MIRAPEX. See the end of this leaflet for a complete list of ingredients in MIRAPEX.

What should I tell my doctor before taking MIRAPEX?

Tell your doctor about all of your medical conditions, including if you

- feel sleepy during the day from a sleep problem other than Restless Legs Syndrome.
- have low blood pressure, or if you feel dizzy or faint, especially when getting up from a lying or sitting position.
- have trouble controlling your muscles (dyskinesia).
- have kidney problems.
- are pregnant or plan to become pregnant. It is not known if MIRAPEX will harm your unborn baby.
- are breast feeding. It is not known if MIRAPEX will pass into your breast milk. You and your doctor should decide if you will take MIRAPEX or breastfeed. You should not do both.
- drink alcohol. Alcohol can increase the chance that MIRAPEX will make you feel sleepy or fall asleep when you should be awake.

Tell your doctor about all the medicines you take, including prescription and non-prescription medicines, vitamins, and herbal supplements. Especially tell your doctor if you take any other medicines that make you sleepy. MIRAPEX and other medicines may interact with each other causing side effects. MIRAPEX may affect the way other medicines work, and other medicines may affect how MIRAPEX works.

How should I take MIRAPEX?

- Take MIRAPEX exactly as your doctor tells you to. Your doctor will tell you how many MIRAPEX tablets to take and when to take them.
- Your doctor may change your dose until you are taking the right amount of medicine to control your symptoms. Do not take more or less MIRAPEX than your doctor tells you to.
- MIRAPEX can be taken with or without food. Taking MIRAPEX with food may lower your chances of getting nausea.
- If you miss a dose, do not double your next dose. Skip the dose you missed and take your next regular dose.
- Be sure to tell your doctor right away if you stop taking MIRAPEX for any reason. Do not start taking MIRAPEX again before speaking with your doctor. If you have Parkinson’s disease and are stopping Mirapex, you should stop Mirapex slowly over 7 days.

What should I avoid while taking MIRAPEX?

- Do not drive a car, operate a machine, or do anything that needs you to be alert until you know how MIRAPEX affects you. See “What is the most important information I should know about MIRAPEX?” at the beginning of this leaflet.
- Do not drink alcohol while taking MIRAPEX. It can increase your chances of feeling sleepy or falling asleep when you should be awake.

What are the possible side effects of MIRAPEX?

MIRAPEX may cause serious side effects, including

- falling asleep during normal daily activities. See “What is the most important information I should know about MIRAPEX?”
- low blood pressure when you sit or stand up quickly. You may have dizziness, nausea, fainting, or sweating. Sit and stand up slowly after you have been sitting or lying down for a while.
- hallucinations. You may see, hear, feel, or taste something that isn’t there. You have a higher chance of having hallucinations if you are over 65 years old.

The most common side effects in people taking MIRAPEX for Restless Legs Syndrome are nausea and sleepiness.

The most common side effects in people taking MIRAPEX for Parkinson’s disease are nausea, dizziness, sleepiness, constipation, hallucinations, insomnia, muscle weakness, confusion, and abnormal movements.

These are not all the possible side effects of MIRAPEX. For more information ask your doctor or pharmacist.

Be sure to talk to your doctor about any side effects that bother you or that do not go away.

Other Information about MIRAPEX
Studies of people with Parkinson’s disease show that they may be at an increased risk of developing melanoma, a form of skin cancer, when compared to people without Parkinson’s disease. It is not known if this problem is associated with Parkinson’s disease or the medicines used to treat Parkinson’s disease. MIRAPEX is one of the medicines used to treat Parkinson’s disease, therefore, patients being treated with MIRAPEX should have periodic skin examinations.

There have been reports of patients taking certain medicines to treat Parkinson’s disease or RLS, including MIRAPEX, that have reported problems with gambling, compulsive eating, compulsive shopping, and increased sex drive. It is not possible to reliably estimate how often these behaviors occur or to determine which factors may contribute to them. If you or your family members notice that you are developing unusual behaviors, talk to your doctor.

How should I store MIRAPEX?

- Store MIRAPEX tablets at room temperature [77°F (25°C)]. Short-term exposure to higher or lower temperatures [from 59°F (15°C) to 86°F (30°C)] is acceptable. Ask your doctor or pharmacist if you have any questions about storing your tablets.
- Keep MIRAPEX out of light.
- Keep MIRAPEX and all medicines out of the reach of children.

General information about MIRAPEX

Medicines are sometimes prescribed for purposes other than those listed in this Patient Information leaflet. Do not take MIRAPEX for a condition for which it was not prescribed. Do not share MIRAPEX with other people, even if they have the same symptoms you do. It may harm them.

This Patient Information leaflet summarizes the most important information about MIRAPEX. For more information, talk with your doctor or pharmacist. They can give you information about MIRAPEX that is written for healthcare professionals. For additional information, you may also call Boehringer Ingelheim Pharmaceuticals, Inc. at 1-800-542-6257, or (TTY) 1-800-459-9906. You may also request information through the company website at http://us.boehringer-ingelheim.com.

What are the ingredients in MIRAPEX?

Active Ingredient: pramipexole dihydrochloride monohydrate

Inactive Ingredients: mannitol, cornstarch, colloidal silicon dioxide, povidone, and magnesium stearate

Distributed by:
Boehringer Ingelheim Pharmaceuticals, Inc.
Ridgefield, CT 06877 USA

Licensed from:
Boehringer Ingelheim International GmbH

Trademark under license from:
Boehringer Ingelheim International GmbH

U.S. Patent Nos. 4,886,812; 6,001,861; and 6,194,445

©2009, Boehringer Ingelheim International GmbH
ALL RIGHTS RESERVED

Rev: April 2009

OT1317PC2409
2001/05

OT1338H
10003128/08

IT1322G
10003129/07

Repackaged by:

Rebel Distributors Corp

Thousand Oaks, CA 91320